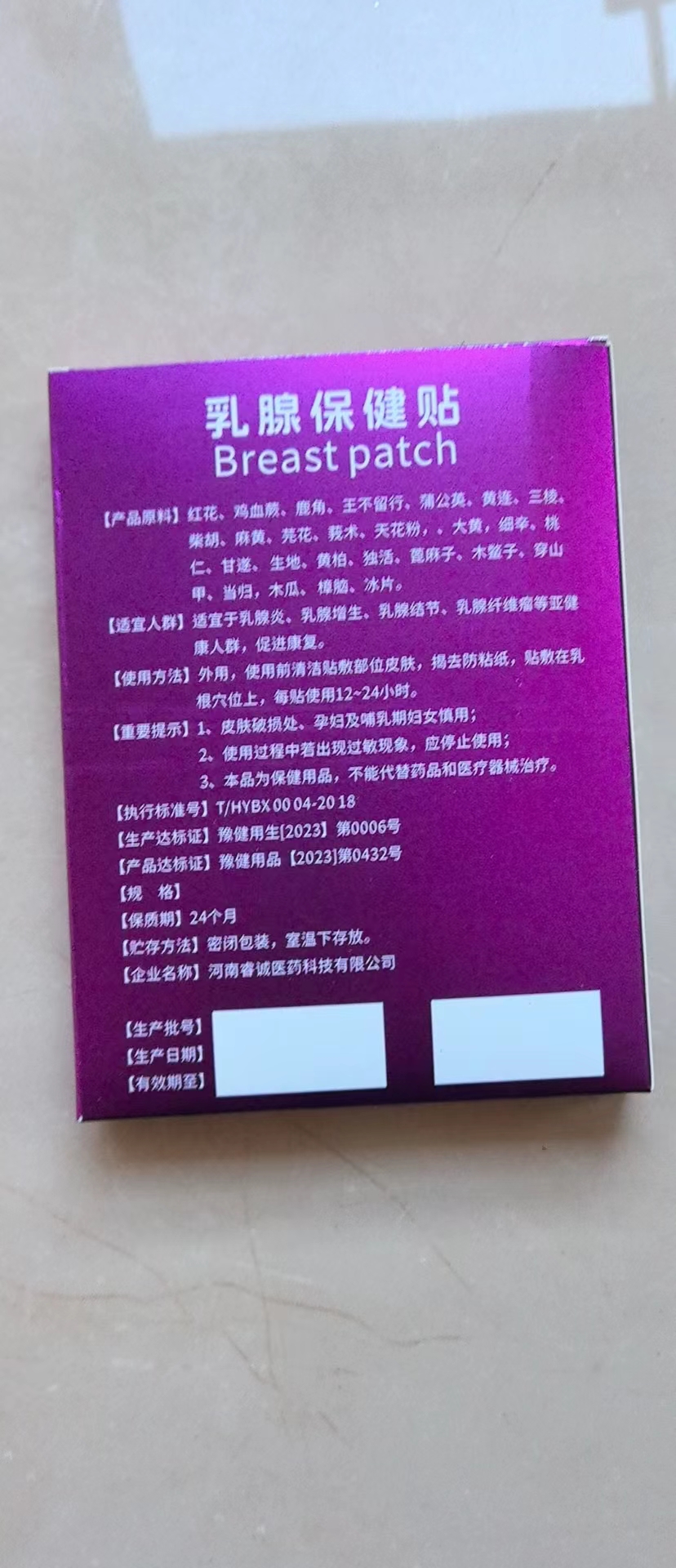 DRUG LABEL: Breast health care patch
NDC: 84852-123 | Form: PATCH
Manufacturer: Jinhua Haimi Bird Trading Co., Ltd
Category: homeopathic | Type: HUMAN OTC DRUG LABEL
Date: 20241030

ACTIVE INGREDIENTS: SAFFLOWER 10 g/100 g
INACTIVE INGREDIENTS: CINNAMOMUM CAMPHORA RESIN; SPATHOLOBUS SUBERECTUS STEM; CERVUS ELAPHUS HORN; BORNEOL; EPHEDRA INTERMEDIA STEM; DAPHNE GENKWA FLOWER BUD; TRICHOSANTHES ROSTHORNII ROOT; ASARUM HETEROTROPOIDES VAR. MANDSHURICUM ROOT; REHMANNIA GLUTINOSA ROOT; CURCUMA PHAEOCAULIS ROOT; RHEUM OFFICINALE ROOT; MOMORDICA COCHINCHINENSIS SEED; MANIS PENTADACTYLA SCALE; GYPSOPHILA VACCARIA SEED; ANGELICA PUBESCENS ROOT; TARAXACUM SINICUM WHOLE; CHAENOMELES LAGENARIA FRUIT; PRUNUS PERSICA SEED; COPTIS TEETA ROOT; SPARGANIUM STOLONIFERUM ROOT; BUPLEURUM CHINENSE ROOT; ANGELICA SINENSIS ROOT; EUPHORBIA KANSUI ROOT; RICINUS COMMUNIS SEED

Breast health care patch

ACTIVE INGREDIENT

Honghua10%

WARNINGS

This product is a health care product, cannot replace drugs and medical equipment treatment

PURPOSE

Suitable for nasal congestion, nasal discomfort of non-health people.

DOSAGE AND ADMINISTRATION

One patch at a time

keep out of reach of children section

INACTIVE INGREDIENT

Jixueteng,lujiao,wangbuliuxing,pugongying,huanglian,sanling,chaihu,mahuang,yuanhua,ezhu,tianhuafen,dahuang,xixin,taoren，gansui,shengdi,huangbo,duhuo,bimazi,mubiezi,chuanshanjia,danggui,mugua,zhangnao,bingpian

INDICATIONS AND USAGE

One patch at a time

PACKAGE LABEL

1